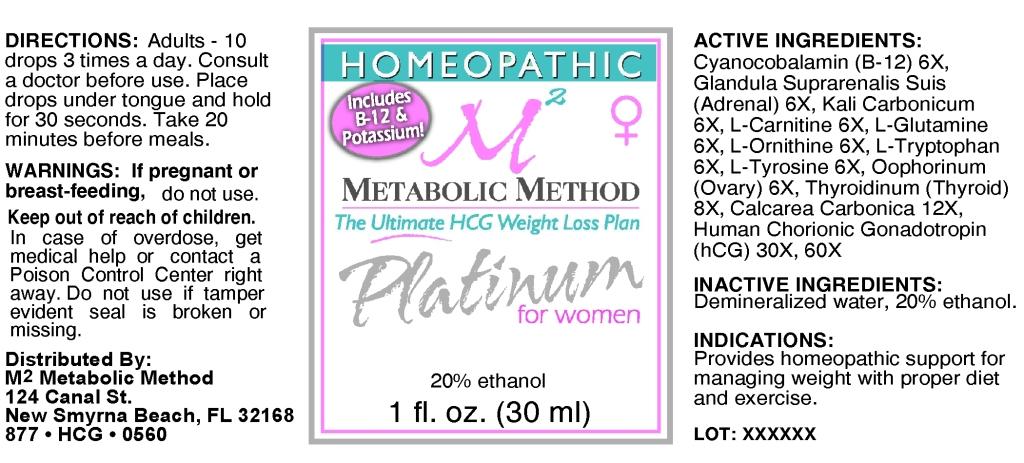 DRUG LABEL: Platinum for Women
NDC: 57520-0647 | Form: LIQUID
Manufacturer: Apotheca Company
Category: homeopathic | Type: HUMAN OTC DRUG LABEL
Date: 20110307

ACTIVE INGREDIENTS: CYANOCOBALAMIN 6 [hp_X]/1 mL; SUS SCROFA ADRENAL GLAND 6 [hp_X]/1 mL; POTASSIUM CARBONATE 6 [hp_X]/1 mL; LEVOCARNITINE 6 [hp_X]/1 mL; GLUTAMINE 6 [hp_X]/1 mL; ORNITHINE 6 [hp_X]/1 mL; TRYPTOPHAN 6 [hp_X]/1 mL; TYROSINE 6 [hp_X]/1 mL; SUS SCROFA OVARY 6 [hp_X]/1 mL; SUS SCROFA THYROID 8 [hp_X]/1 mL; OYSTER SHELL CALCIUM CARBONATE, CRUDE 12 [hp_X]/1 mL; HUMAN CHORIONIC GONADOTROPIN 60 [hp_X]/1 mL
INACTIVE INGREDIENTS: WATER; ALCOHOL

Platinum for Women

ACTIVE INGREDIENT

ACTIVE INGREDIENTS: Cyanocobalamin (B-12) 6X, Glandula suprarenalis suis (Adrenal) 6X, Kali carbonicum 6X, L-carnitine 6X, L-glutamine 6, L-ornithine 6X, L-tryptophan 6X, L-tyrosine 6X, Oophorinum (Ovary) 6X, Thyroidinum (Thyroid) 8X, Calcarea carbonica 12X, Human chorionic gonadotropin (hCG) 30X, 60X.

PURPOSE

INDICATIONS: Provides homeopathic support for managing weight with proper diet and exercise.

WARNINGS

WARNINGS: If pregnant or breast-feeding, do not use.

Keep out of reach of children. In case of overdose, get medical help or contact a Poison Control Center right away.

Do not use if tamper evident seal is broken or missing.

DOSAGE AND ADMINISTRATION

DIRECTIONS: Adults - 10 drops 3 times a day. Consult a doctor before use. Place drops under tongue and hold for 30 seconds. Take 20 minutes before meals.

INACTIVE INGREDIENTS: Demineralized water, 20% Ethanol.

KEEP OUT OF REACH OF CHILDREN. In case of overdose, get medical help or contact a Poison Control Center right away.

INDICATIONS AND USAGE

INDICATIONS: Provides homeopathic support for managing weight with proper diet and exercise.

QUESTIONS

Distributed By:

M2 Metabolic Method

124 Canal St.

New Smyrna Beach, FL 32168

877-HCG-0560

PACKAGE LABEL

HOMEOPATHIC

Includes B-12 and Potassium!

METABOLIC METHOD

The Ultimate HCG Weight Loss Plan

Platinum for Women

1 fl oz. (30 ml)